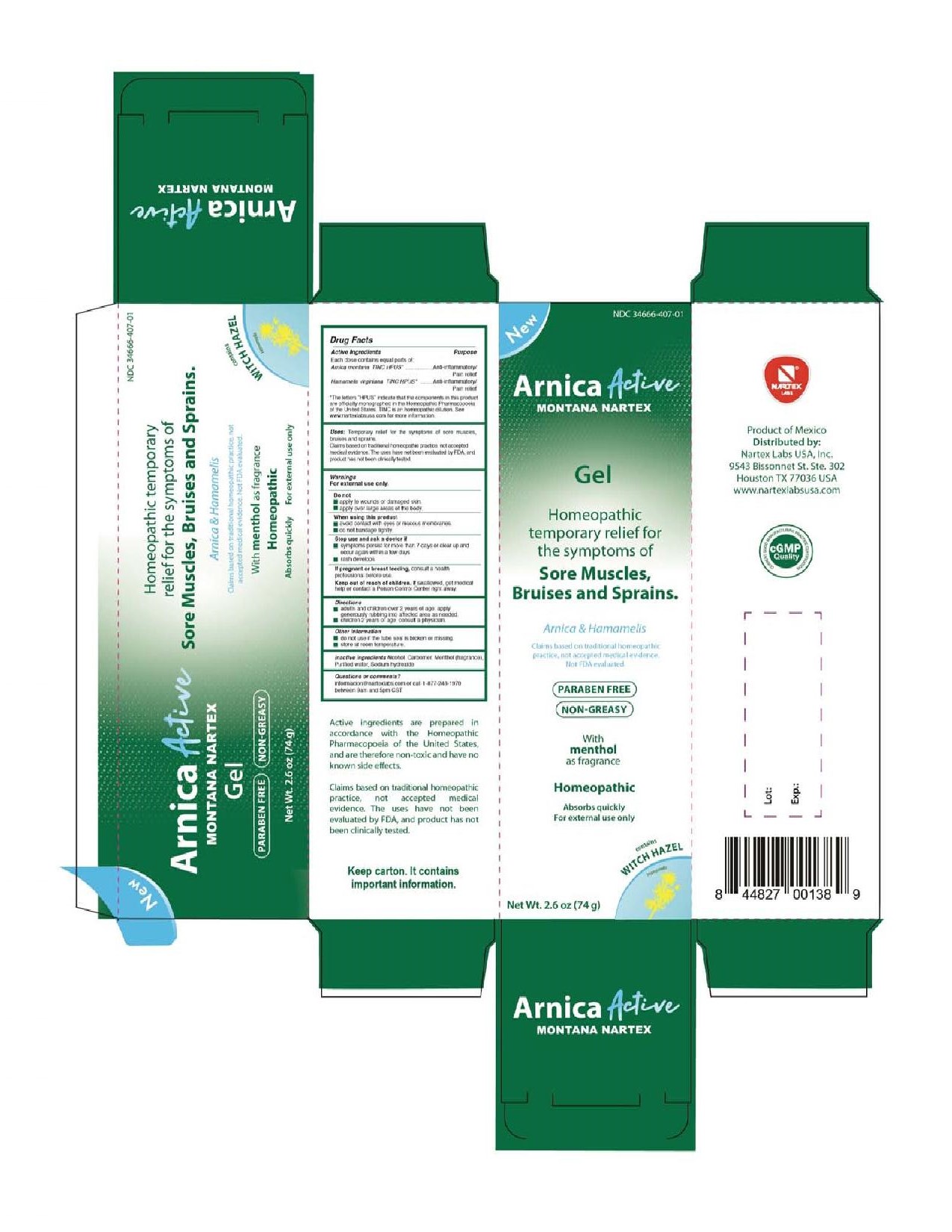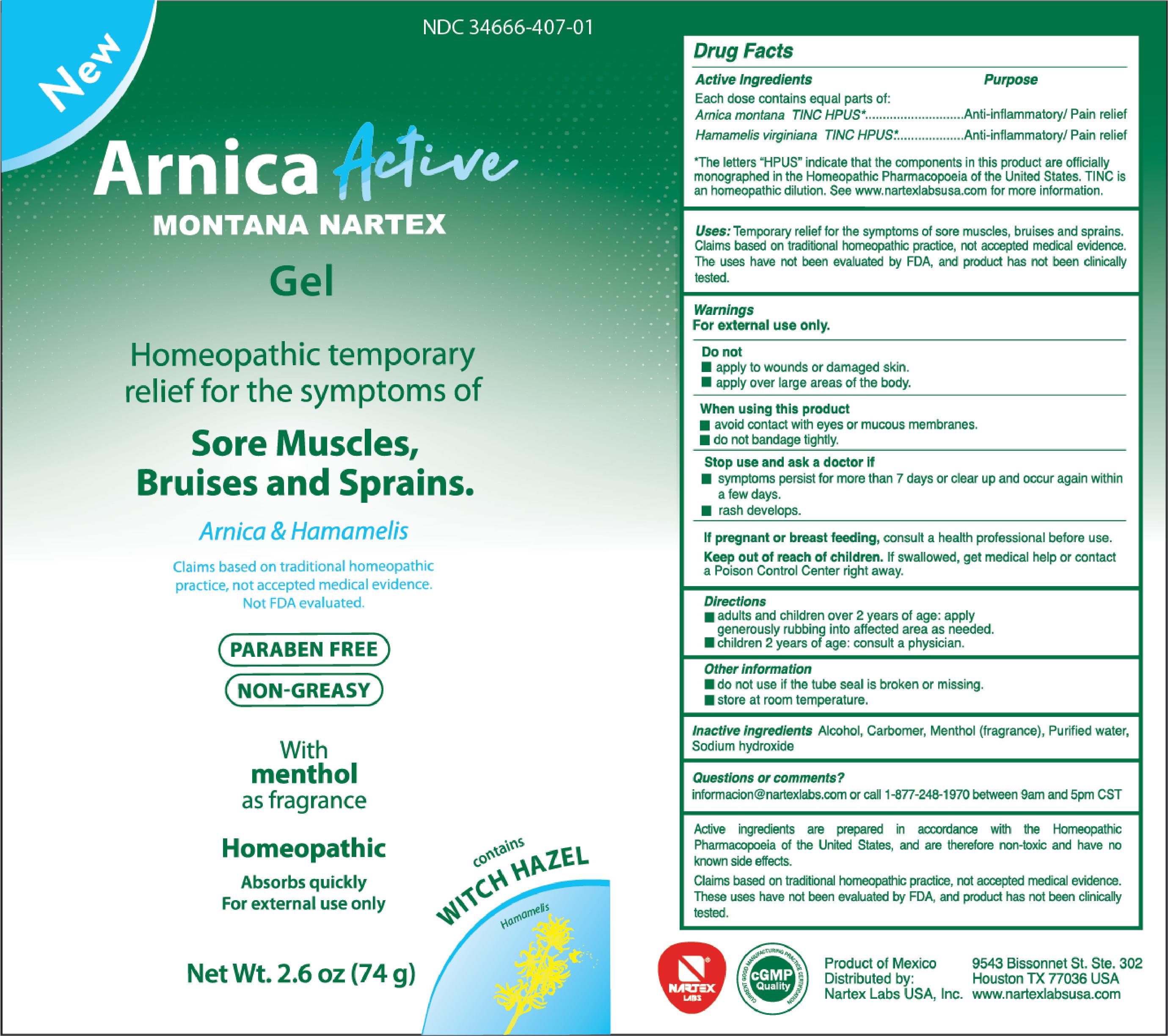 DRUG LABEL: Arnica Active Montana Nartex
NDC: 34666-407 | Form: GEL
Manufacturer: Nartex Laboratorios Homeopaticos, S.A. de C.V.
Category: homeopathic | Type: HUMAN OTC DRUG LABEL
Date: 20211230

ACTIVE INGREDIENTS: ARNICA MONTANA 1 [hp_X]/74 g; HAMAMELIS VIRGINIANA ROOT BARK/STEM BARK 1 [hp_X]/74 g
INACTIVE INGREDIENTS: ALCOHOL; MENTHOL; SODIUM HYDROXIDE; CARBOMER HOMOPOLYMER, UNSPECIFIED TYPE; WATER

Arnica Active Montana Nartex

Active ingredients

Each dose contains equal parts of:

Arnica montana TINC HPUS*

Hamamelis virginia TINC HPUS*

*The letters "HPUS" indicate that the components in this product are officially monographed in the Homeopathic Pharmacopoeia of the United States. TINC is an homeopathic dilution. See www.nartexlabsusa.com for more information.

Purpose

Each dose contains equal parts of:

Arnica montana TINC HPUS*..................Anti-inflammatory/Pain relief

Hamamelis virginia TINC HPUS*.........................Anti-inflammatory/Pain relief

*The letters "HPUS" indicate that the components in this product are officially monographed in the Homeopathic Pharmacopoeia of the United States. TINC is an homeopathic dilution. See www.nartexlabsusa.com for more information.

Uses

Temporary relief for the symptoms of sore muscles, bruises and sprains.

Claims based on traditional homeopathic practice, not accepted medical evidence. The uses have not been evaluated by FDA, and product has not been clinically tested.

Warnings

For external use only.

Warnings

Do not

- apply to wounds or damaged skin
- apply over large areas of the body

When using this product

- avoid contact with eyes or mucous membranes
- do not bandage tightly

Stop use and ask a doctor if

- symptoms persist for more than 7 days or clear up and occur again within a few days
- rash develops

PREGNANCY OR BREAST FEEDING

If pregnant or breast feeding, consult a health professional before use.

Keep out of reach of children. If swallowed, get medical help or contact a Poison Control Center right away.

Directions

- adults and children over 2 years of age: apply generously rubbing into affected area as needed.
- children 2 years of age: consult a physician.

Other information

- do not use if the tube seal is broken or missing
- store at room temperature

Inactive ingredients

Alcohol, Carbomer, Menthol (fragrance), Purified water, Sodium hydroxide

Questions or comments?

informacion@nartexlabs.com or call 1-877-248-1970 between 9am and 5pm CST

PACKAGE LABEL

New

NDC 34666-407-01

Arnica Active Montana Nartex

Gel

Homeopathic temporary relief for the symptoms of Sore Muscles, Bruises and Sprains.

Arnica & Hamamelis

Claims based on traditional homeopathic practice, not accepted medical evidence. Not FDA evaluated.

Paraben Free

Non-Greasy

With menthol as fragrance

Homeopathic

Absorbs quickly

For external use only

contains Witch Hazel

Hamamelis

Net Wt. 2.6 oz (74 g)